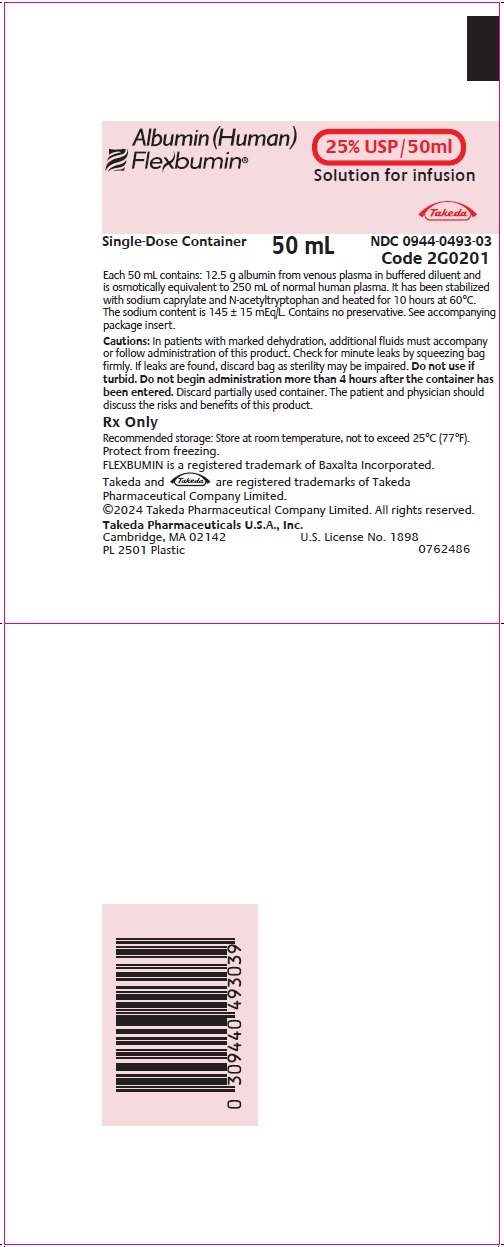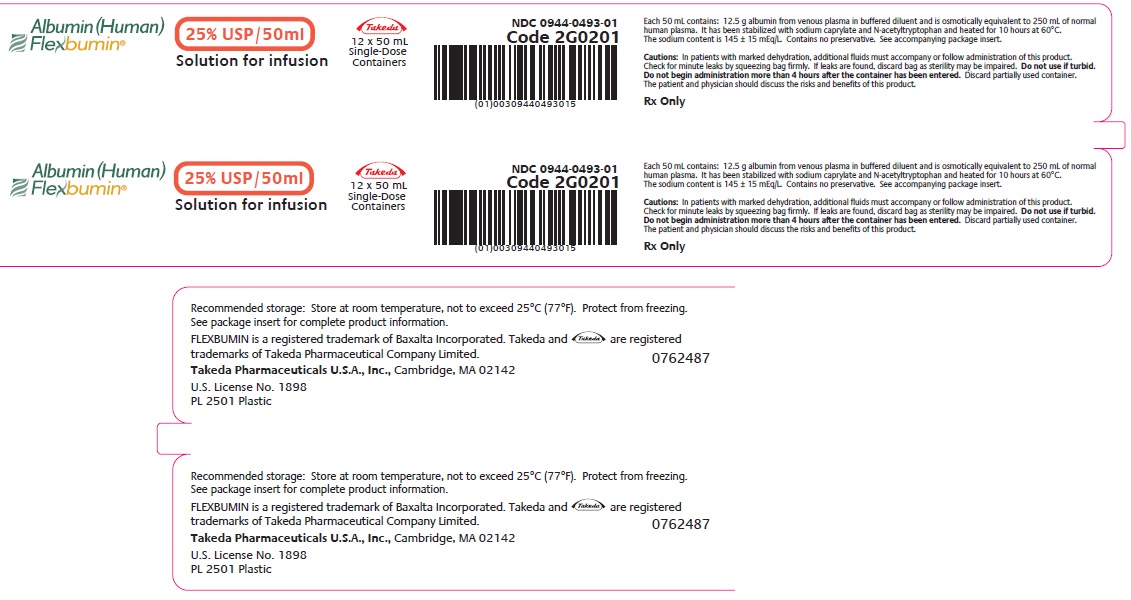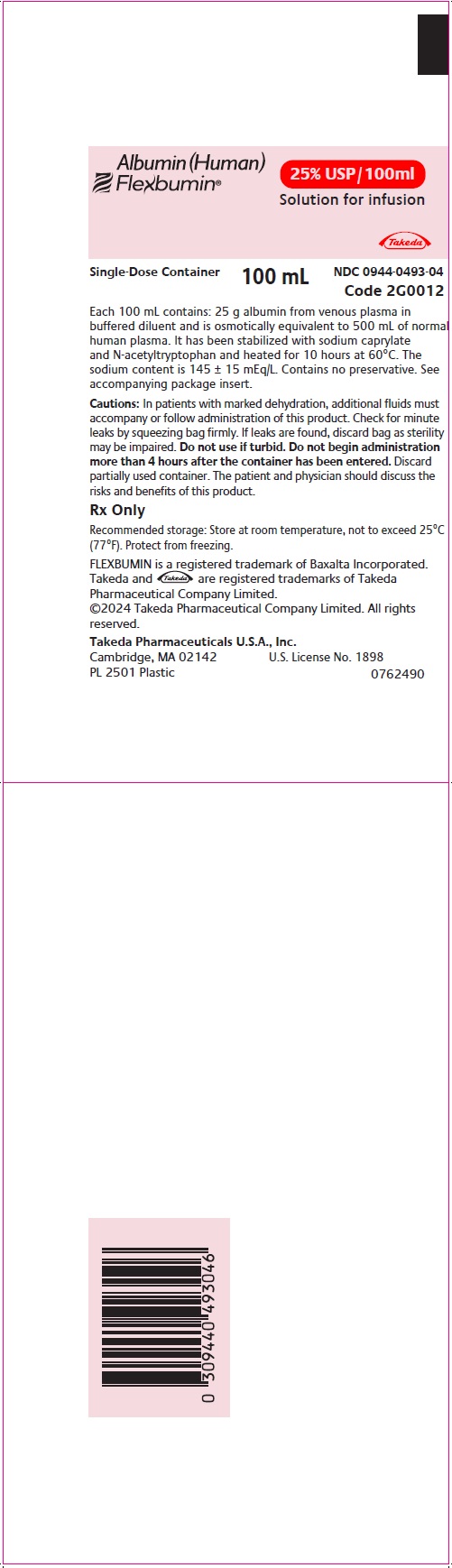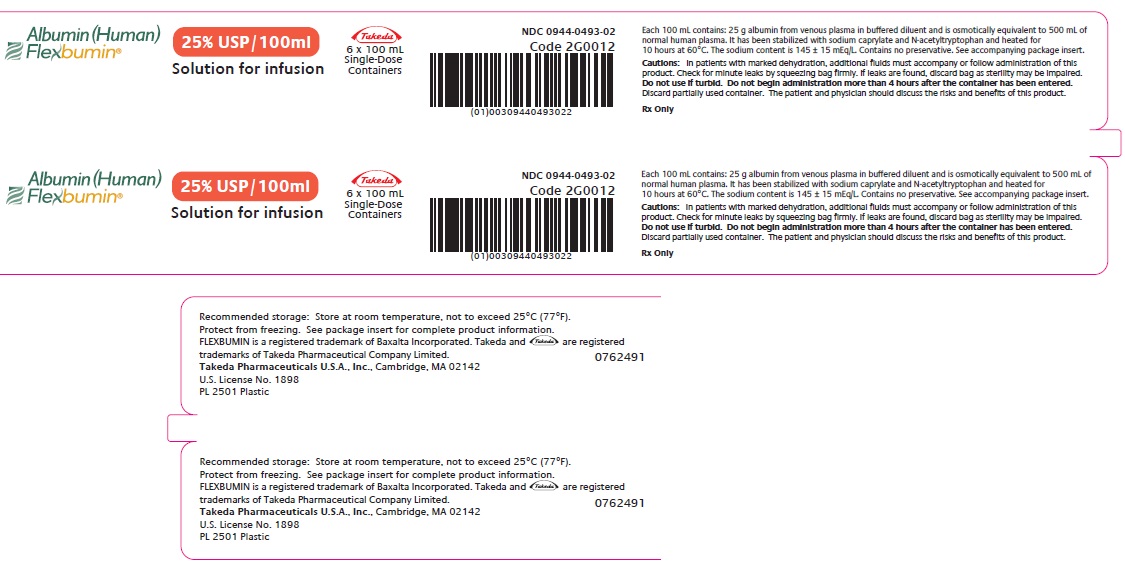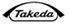 DRUG LABEL: FLEXBUMIN
NDC: 0944-0493 | Form: SOLUTION
Manufacturer: Takeda Pharmaceuticals America, Inc.
Category: other | Type: PLASMA DERIVATIVE
Date: 20241218

ACTIVE INGREDIENTS: ALBUMIN HUMAN 0.25 g/1 mL
INACTIVE INGREDIENTS: N-ACETYL-DL-TRYPTOPHAN SODIUM; SODIUM CAPRYLATE; SODIUM CATION

HIGHLIGHTS OF PRESCRIBING INFORMATION

These highlights do not include all the information needed to use FLEXBUMIN® 25% safely and effectively. See full prescribing information for FLEXBUMIN 25%.
FLEXBUMIN® 25% Albumin (Human), USP, 25% Solution,
for intravenous use
Initial U.S. Approval: 2005

1 INDICATIONS AND USAGE

FLEXBUMIN 25%, Albumin (Human) Solution is indicated for:

- Hypovolemia (1.1)
- Hypoalbuminemia: Burns, Adult Respiratory Distress Syndrome (ARDS) and Nephrosis (1.2)
- Cardiopulmonary Bypass Surgery (1.3)
- Hemolytic Disease of the Newborn (HDN) (1.4)

Limitations of Use: Albumin is not indicated as an intravenous nutrient. (1.5)

2 DOSAGE AND ADMINISTRATION

For intravenous use only.

- Adjust dose and rate of infusion based on the patient's clinical status. (2.1)
- Do not exceed 2 g of albumin per kg body weight for the daily dose. (2.1)
- Do not exceed 1 mL/min for patients with normal blood volume. (2.1)
- Do not dilute with Sterile Water for Injection. (2.2)

Indication | Dose
Hypovolemic Shock | Infants and young children: 2.5 to 5 mL per kg body weight. Older children and adults: initial dose 100 to 200 mL. Repeat after 15 to 30 minutes if the response is not adequate.
Hypoalbuminemia | Calculate the body albumin compartment to be 80 to 100 mL per kg body weight. Do not exceed a daily dose of 2 g of albumin per kg of body weight.
Burns | The dosage should be determined according to the patient's condition and response to treatment after the first 24 hours.
Hemolytic Disease of the Newborn | 1 g per kg body weight prior to or during exchange transfusion.^12

3 DOSAGE FORMS AND STRENGTHS

FLEXBUMIN 25% is a solution containing 25 g of albumin per each 100 mL.

4 CONTRAINDICATIONS

- History of hypersensitivity reaction to albumin preparations or to any of the excipients (N-acetyltryptophan and sodium caprylate). (4)
- Severe anemia or cardiac failure with normal or increased intravascular volume. (4)

5 WARNINGS AND PRECAUTIONS

- Hypersensitivity reactions (including anaphylactic reactions) have been observed. If hypersensitivity reaction is suspected, discontinue use and implement appropriate standard medical treatment. (5.1)
- Under conditions where hypervolemia and/or hemodilution may occur, adjust the dose and rate of infusion to the patient's volume status. When administering large volumes, monitor hemodynamic parameters and ensure adequate substitution of other blood constituents are available (coagulation factors, platelets, and erythrocytes). Monitor electrolyte balance. (5.2)
- Closely monitor hemodynamic parameters after administration for evidence of cardiac or respiratory failure, renal failure or increasing intracranial pressure. (5.3)
- Monitor blood pressure in trauma patients and postoperative surgery patients in order to detect re-bleeding secondary to clot disruption. (5.4)
- Do not dilute with Sterile Water for Injection as this can cause hemolysis in recipients. (5.5)
  This product is made from human plasma and may contain infectious agents e.g., viruses and, theoretically, the variant Creutzfeldt-Jakob disease agent. (5.6)

6 ADVERSE REACTIONS

The most serious adverse reactions are hypersensitivity reaction (including anaphylactic reaction) and pulmonary edema. (6)

To report SUSPECTED ADVERSE REACTIONS, contact Takeda Pharmaceuticals U.S.A., Inc. at 1-877-TAKEDA-7 (1-877-825-3327) or contact the FDA at 1-800-FDA-1088 or www.fda.gov/medwatch.

8 USE IN SPECIFIC POPULATIONS

Pediatric Use: Ensure dose is appropriate for body weight. (8.4)

FULL PRESCRIBING INFORMATION

1 INDICATIONS AND USAGE

FLEXBUMIN® 25% [Albumin (Human)] is indicated for hypovolemia, hypoalbuminemia, cardiopulmonary bypass surgery, and hemolytic disease of the newborn (HDN).

1.1 Hypovolemia

FLEXBUMIN 25% [Albumin (Human)] is indicated for reversing hypovolemia. When hypovolemia is long standing and hypoalbuminemia exists accompanied by adequate hydration or edema, 25% albumin should be used.^4,6

1.2 Hypoalbuminemia

FLEXBUMIN 25% is indicated for patients with hypoalbuminemia resulting from one or more of the following:^5

(1) Inadequate production (e.g., malnutrition, burns, major injury, infections)
(2) Excessive catabolism (e.g., burns, major injury, pancreatitis)
(3) Loss from the body (e.g., hemorrhage, excessive renal excretion, burn exudates)
(4) Redistribution within the body (e.g., major surgery, various inflammatory conditions)

FLEXBUMIN 25% is indicated for patients with hypoalbuminemia accompanying severe injuries, infections or severe pancreatitis that cannot be quickly reversed and nutritional supplements fail to restore serum albumin levels.

Burns

After the first 24 hours, FLEXBUMIN 25% is indicated, in conjunction with appropriate crystalloid therapy, for the treatment of oncotic deficits following extensive burns and to replace the protein loss which accompanies any severe burn.^4,6

Adult Respiratory Distress Syndrome (ARDS)

FLEXBUMIN 25% is indicated, in conjunction with diuretics, to correct interstitial pulmonary edema and hypoproteinemia associated with ARDS.^4

Nephrosis

FLEXBUMIN 25% is indicated for treatment of edema in patients with severe nephrosis who are receiving steroids and/or diuretics.

1.3 Cardiopulmonary Bypass Surgery

Preoperative dilution of blood using albumin and crystalloid can be used in cardiopulmonary bypass surgery. FLEXBUMIN 25% is indicated as a component of the pump priming during cardiopulmonary bypass procedures.^4,6,12

1.4 Hemolytic Disease of the Newborn (HDN)

FLEXBUMIN 25% is indicated for infants with severe HDN to bind and detoxify unconjugated bilirubin.

1.5 Limitations of Use

Albumin is not indicated as an intravenous nutrient.

2 DOSAGE AND ADMINISTRATION

For intravenous use only.

2.1 Dose

The dose required depends on the patient's body weight, severity of injury/illness and on continuing fluid and protein losses. Adjust the concentration, dosage and infusion rate to the patient's individual requirements. Use adequacy of circulating blood volume, not plasma albumin levels, to determine the dose required. Refer to Table 1 for recommended doses.

Do not exceed 2 g of albumin per kg of body weight for the daily dose. Do not exceed 1 mL/min for patients with normal blood volume. More rapid administration can cause circulatory overload and pulmonary edema^11 [see Warnings and Precautions (5.2)].

Table 1: Recommended Dose
Indication | Dose
Hypovolemic Shock | Infants and young children: 2.5 to 5 mL per kg body weight. Older children and adults: initial dose 100 to 200 mL. Repeat after 15 to 30 minutes if response is not adequate.
Hypoalbuminemia | Calculate the body albumin compartment to be 80 to 100 mL per kg body weight. Do not exceed a daily dose of 2 g of albumin per kg of body weight.
Burns | The dosage should be determined according to the patient's condition and response to treatment after the first 24 hours.
Hemolytic disease in newborn | 1 g per kilogram body weight prior to or during exchange transfusion.^12

Hypovolemia

Reversing hypovolemia depends largely upon its ability to draw interstitial fluid into the circulation. It is most effective in patients who are well hydrated. Use 5% protein solutions or dilute 25% albumin with crystalloid solutions in the absence of adequate or excessive hydration.

Hypoalbuminemia

If albumin deficit is the result of excessive protein loss, the effect of FLEXBUMIN 25% will be temporary unless the underlying disorder is reversed.

2.2 Administration

- Visually inspect parenteral drug product for particulate matter and discoloration prior to administration. FLEXBUMIN 25% is a transparent or slightly opalescent solution, which may have a greenish tint or may vary from a pale straw to an amber color. Do not use unless solution is clear of particulate matter or if the solution is turbid.
- Check the container for minute leaks prior to use by squeezing the bag firmly. If leaks are found, discard solution.
- Do not use the bag if the tip protector is damaged, detached or missing.
- Do not dilute with Sterile Water for Injection. Acceptable diluents include 0.9% Sodium Chloride or 5% Dextrose in Water [see Warnings and Precautions (5.5)].
- Do not mix or add with other medicinal products including blood and blood components, protein hydrolysates or solutions containing alcohol. Do not add supplementary medication.
- Administer within 4 hours after the container has been entered.
- Monitor hemodynamic parameters in patients receiving FLEXBUMIN 25% and check for the risk of hypervolemia and cardiovascular overload [see Warnings and Precautions (5.2)].
- Record the name and batch number of the product to maintain a link between the patient and the product.
- Discard unused portion.

CAUTION: Do not use plastic containers in series connections. Such use could result in air embolism due to residual air being drawn from the primary container before the administration of fluid from the secondary container is complete.

1. Suspend container from eyelet support.
2. Remove plastic protector from outlet port at bottom of container.
3. Attach administration set. Refer to complete directions accompanying the administration set.

3 DOSAGE FORMS AND STRENGTHS

FLEXBUMIN 25% is a solution containing 25 g of albumin per 100 mL.

4 CONTRAINDICATIONS

- Patients with a history of hypersensitivity reaction to albumin preparations or to any of the excipients (N-acetyltryptophan and sodium caprylate). Reactions have included anaphylactic shock, anaphylactic reaction, or hypersensitivity/allergic reactions [see Warnings and Precautions (5.1), Adverse Reactions (6.2)].
- Patients with severe anemia or cardiac failure with normal or increased intravascular volume [see Warnings and Precautions (5.2)].

5 WARNINGS AND PRECAUTIONS

5.1 Hypersensitivity Reactions

Hypersensitivity reactions (including anaphylactic reactions) have been observed. Discontinue administration immediately if a hypersensitivity reaction (including anaphylactic type reactions) is suspected. In case of shock, implement standard medical treatment for shock.

5.2 Hypervolemia/Hemodilution

Under conditions where hypervolemia and/or hemodilution may occur, adjust dose and rate of infusion to the patient's volume status. Monitor coagulation and hematology parameters when comparatively large volumes are replaced. Ensure adequate substitution of other blood constituents (coagulation factors, platelets, and erythrocytes). Monitor electrolyte status to maintain the electrolyte balance.

Discontinue administration at the first clinical signs of cardiovascular overload (e.g., headache, dyspnea, jugular venous distention, rales and abnormal elevations in systemic or central venous blood pressure).

Conditions that pose increased risk of hypervolemia and/or hemodilution include but are not limited to:

- Heart failure
- Hypertension
- Esophageal varices
- Pulmonary edema
- Hemorrhagic diathesis
- Severe anemia
- Renal failure

5.3 Hemodynamics

Closely monitor hemodynamic parameters after administering FLEXBUMIN 25% for evidence of cardiac or respiratory failure, renal failure, or increasing intracranial pressure.

5.4 Blood Pressure

Monitor blood pressure in trauma patients and postoperative surgery patients resuscitated with FLEXBUMIN 25% in order to detect re-bleeding secondary to clot disruption.

5.5 Hemolysis

Do not dilute FLEXBUMIN 25% with Sterile Water for Injection as this can cause hemolysis in recipients. There exists a risk of potentially fatal hemolysis and acute renal failure from the use of Sterile Water for Injection as a diluent for Albumin (Human) in concentrations of 20% or higher [see Dosage and Administration (2.2)].

5.6 Transmission of Infectious Agents

FLEXBUMIN 25% is a derivative of human blood. Based on effective donor screening and product manufacturing processes, it carries an extremely remote risk for transmission of viral diseases and variant Creutzfeldt-Jakob disease (vCJD). There is a theoretical risk for transmission of Creutzfeldt-Jakob disease (CJD), but if that risk actually exists, the risk of transmission would also be considered extremely remote. No cases of transmission of viral diseases, CJD or vCJD, have ever been identified for licensed albumin.

All infections thought by a physician possibly to have been transmitted by this product should be reported by the physician or other healthcare provider to Takeda Pharmaceuticals U.S.A., Inc. at 1-877-TAKEDA-7 (1-877-825-3327). The physician should discuss the risks and benefits of this product with the patient.

6 ADVERSE REACTIONS

The most serious adverse reactions are hypersensitivity reaction (including anaphylactic reaction) and pulmonary edema.

6.1 Clinical Trials Experience

No sponsor initiated clinical studies have been conducted with FLEXBUMIN 25%.

6.2 Postmarketing Experience

The following adverse reactions have been identified during postapproval use of FLEXBUMIN 25%. Because these reactions are reported voluntarily from a population of uncertain size, it is not always possible to reliably estimate their frequency or establish a causal relationship to drug exposure.

The following adverse reactions have been reported in the postapproval use of FLEXBUMIN 25%:

- Immune System Disorders: Anaphylactic shock, anaphylactic reaction, hypersensitivity/allergic reactions
- Nervous System Disorders: Headache, dysgeusia
- Cardiac Disorders: Myocardial infarction, atrial fibrillation, tachycardia
- Vascular Disorders: Hypotension, flushing
- Respiratory, Thoracic, and Mediastinal Disorders: Pulmonary edema, dyspnea
- Gastrointestinal Disorders: Vomiting, nausea
- Skin and Subcutaneous Tissue Disorders: Urticaria, rash, pruritus
- General Disorders and Administration Site Conditions: Pyrexia, chills

8 USE IN SPECIFIC POPULATIONS

8.1 Pregnancy

Risk Summary

No human or animal data are available to indicate the presence or absence of drug-associated risk. It is not known whether FLEXBUMIN 25% can cause fetal harm when administered to a pregnant woman or can affect reproductive capacity.

8.2 Lactation

Risk Summary

No human or animal data are available to indicate the presence or absence of drug-associated risk. It is not known whether FLEXBUMIN 25% is excreted in human milk.

8.4 Pediatric Use

The safety of albumin solutions has been demonstrated in children provided the dose is appropriate for body weight; however, the safety of FLEXBUMIN 25% has not been evaluated in sponsor conducted pediatric studies.

8.5 Geriatric Use

No human or animal data.

10 OVERDOSAGE

Hypervolemia may occur if the dosage and rate of infusion are too high [see Warnings and Precautions (5.2)].

11 DESCRIPTION

FLEXBUMIN 25% is a sterile, nonpyrogenic preparation of albumin in a single dosage form for intravenous administration. Each 100 mL contains 25 g of albumin. It has been adjusted to physiological pH with sodium bicarbonate and/or sodium hydroxide and stabilized with N-acetyltryptophan (0.02M) and sodium caprylate (0.02M). The sodium content is 145 ± 15 mEq/L. FLEXBUMIN 25% contains no preservative and none of the coagulation factors found in fresh whole blood or plasma. FLEXBUMIN 25% is a transparent or slightly opalescent solution which may have a greenish tint or may vary from a pale straw to an amber color and is clear of particulate matter.

FLEXBUMIN 25% is manufactured from human plasma by the modified Cohn-Oncley cold ethanol fractionation process, which includes a series of cold-ethanol precipitation, centrifugation and/or filtration steps followed by pasteurization of the final product at 60 ± 0.5°C for 10 to 11 hours. This process accomplishes both purification of albumin and reduction of viruses.

In vitro studies demonstrate that the manufacturing process for FLEXBUMIN 25% provides for effective viral reduction. These viral reduction studies, summarized in Table 2, demonstrate viral clearance during the manufacturing process for FLEXBUMIN 25%.

These studies indicate that specific steps in the manufacturing of FLEXBUMIN 25% are capable of eliminating/inactivating a wide range of relevant and model viruses. Since the mechanism of virus elimination/inactivation by fractionation and by heating steps is different, the overall manufacturing process of FLEXBUMIN 25% is effective in reducing viral load.

Table 2: Summary of Viral Reduction Factor for Each Virus and Processing Step [Human immunodeficiency virus, type 1 (HIV-1) both as a target virus and model for HIV-2 and other lipid-enveloped RNA viruses; bovine viral diarrhea virus (BVDV), a model for lipid-enveloped RNA viruses, such as hepatitis C virus (HCV); West Nile Virus (WNV), a target virus and model for other similar lipid-enveloped RNA viruses; pseudorabies virus (PRV), a model for other lipid-enveloped DNA viruses such as hepatitis B virus (HBV); mice minute virus (MMV), models for non-enveloped DNA viruses such as human parvovirus B19^10; and hepatitis A virus (HAV), a target virus and a model for other non-enveloped RNA viruses.]
Process Step | Viral Reduction Factor (log10)
Process Step | Lipid Enveloped |  |  |  | Non-Enveloped
 | HIV-1 | Flaviviridae |  | PRV | HAV | Parvoviridae
 | HIV-1 | BVDV | WNV | PRV | HAV | MMV
Processing of Fraction I + II + III/II + III supernatant to Fraction IV4 Cuno 70C filtrate [Other Albumin fractionation process steps (processing of cryo-poor plasma to Fraction I + II + III/II + III supernatant and processing of Fraction V suspension to Cuno 90LP filtrate) showed virus reduction capacity in in vitro viral clearance studies. These process steps also contribute to the overall viral clearance effectiveness of the manufacturing process. However, since the mechanism of virus removal is similar to that of this particular process step, the viral inactivation data from other steps were not used in the calculation of the Mean Cumulative Reduction Factor.] | >4.9 | >4.8 | >5.7 | >5.5 | >4.5 | 3.0
Pasteurization | >7.8 | >6.5 | n.d. [n.d. = not determined.] | >7.4 | 3.2 | 1.6 [Recent scientific data suggests that the actual human parvovirus B19 (B19V) is far more effectively inactivated by pasteurization than indicated by model virus data.^10]
Mean Cumulative Reduction Factor, log10 | >12.7 | >11.3 | >5.7 | >12.9 | >7.7 | 4.6

The likelihood of the presence of viable hepatitis viruses has been minimized by testing the plasma at three stages: for the presence of hepatitis viruses, by fractionation steps with demonstrated virus removal capacity and by heating the product for 10 hours at 60°C. This procedure has been shown to be an effective method of inactivating hepatitis virus in albumin solutions even when those solutions were prepared from plasma known to be infective.^1,2,3

12 CLINICAL PHARMACOLOGY

12.1 Mechanism of Action

Albumin is responsible for 70 to 80% of the colloid osmotic pressure of normal plasma, thus making it useful in regulating the volume of circulating blood.^4,5,6 Albumin is also a transport protein and binds naturally occurring, therapeutic and toxic materials in the circulation.^5,6

12.2 Pharmacodynamics

FLEXBUMIN 25% is osmotically equivalent to approximately five times its volume of human plasma. When injected intravenously, 25% albumin will draw about 3.5 times its volume of additional fluid into the circulation within 15 minutes, except when the patient is markedly dehydrated. This extra fluid reduces hemoconcentration and blood viscosity. The degree and duration of volume expansion depends upon the initial blood volume. In patients with decreased blood volume, the effect of infused albumin can persist for many hours; however, in patients with normal blood volume, the duration will be shorter.^7,8,9

12.3 Pharmacokinetics

Total body albumin is estimated to be 350 g for a 70 kg patient, with more than 60% located in the extravascular fluid compartment. The half-life of albumin is 15 to 20 days with a turnover of approximately 15 g per day.^5

The minimum plasma albumin level necessary to prevent or reverse peripheral edema is unknown. It is recommended that plasma albumin levels be maintained at approximately 2.5 g/dL. This concentration provides a plasma oncotic pressure value of 20 mmHg.^4

15 REFERENCES

1. Cai K, Gierman T, Hotta J, et al: Ensuring the Biologic Safety of Plasma-Derived Therapeutic Proteins. Biodrugs 2005; 19 (2): 79-96.
2. Gerety R, Aronson D: Plasma derivatives and viral hepatitis. Transfusion 1982; 22 (5): 347-351.
3. Burnouf T, Padilla A: Current strategies to prevent transmission of prions by human plasma derivatives. Transfusion Clinique et Biologique 2006; 13: 320-328.
4. Tullis J: Albumin 1. Background and use Albumin 2. Guidelines for clinical use. JAMA 1977; 237 (4): 355-360; 460-463.
5. Peters T Jr: Serum albumin. The Plasma Proteins, 2nd Edition, Vol 1. Putnam FW (ed). New York, Academic Press, 1975, pp 133-181.
6. Finlayson J: Albumin products. Seminars in Thrombosis and Hemostasis 1980; 6 (2): 85-120.
7. Haynes G, Navickis R, Wilkes M: Albumin administration – what is the evidence of clinical benefit? A systematic review of randomized controlled trials. European Journal of Anesthesiology 2003; 20: 771-793.
8. Mendez C, McClain C, Marsano L, et al: Albumin Therapy in Clinical Practice. Nutrition in Clinical Practice 2005; 20:314-320.
9. Quinlan G, Martin G, Evans T: Albumin: Biochemical Properties and Therapeutic Potential. Hepatology 2005; 41 (6): 1211-1219.
10. Blümel J, Schmidt I, Willkommen H, et al: Inactivation of parvovirus B19 during pasteurization of human serum albumin. Transfusion 2002; 42:1011-1018.
11. Grocott M, Mythen M, Gan T: Perioperative Fluid Management and Clinical Outcomes in Adults. Anesth Analg. 2005; 100: 1093-1106.
12. Tsao Y, Yu V: Albumin in management of neonatal hyperbilirubinaemia. Archives of Disease in Childhood 1972; 47: 250.

16 HOW SUPPLIED/STORAGE AND HANDLING

FLEXBUMIN 25% is supplied in a single-dose plastic container:

Plastic Container NDC Number | Carton NDC Number | Grams Protein and Fill Size
NDC 0944-0493-03 (quantity of 1) | NDC 0944-0493-01 (quantity of 12) | 12.5 grams in a 50 mL plastic container
NDC 0944-0493-04 (quantity of 1) | NDC 0944-0493-02 (quantity of 6) | 25 grams in a 100 mL plastic container

Storage

Room temperature: not to exceed 25°C (77°F). Protect from freezing.

17 PATIENT COUNSELING INFORMATION

- Inform patients of the early signs of hypersensitivity reactions, including hives, generalized urticaria, chest tightness, dyspnea, wheezing, faintness, hypotension, and anaphylaxis [see Warnings and Precautions (5.1)].
- Inform patients that FLEXBUMIN 25% is made from human plasma and may contain infectious agents that can cause disease (e.g., viruses and, theoretically, the CJD agent). Explain that the risk of FLEXBUMIN 25% transmitting an infectious agent has been reduced by screening the plasma donors, by testing the donated plasma for certain virus infections, and by a process demonstrated to inactivate and/or remove certain viruses during manufacturing. Symptoms of a possible virus infection include headache, fever, nausea, vomiting, weakness, malaise, diarrhea, or, in the case of hepatitis, jaundice [see Warnings and Precautions (5.6)].

Takeda Pharmaceuticals U.S.A., Inc.
Cambridge, MA 02142
U.S. License No. 1898

FLEXBUMIN is a registered trademark of Baxalta Incorporated.
Takeda and are registered trademarks of Takeda Pharmaceutical Company Limited.

©2024 Takeda Pharmaceutical Company Limited. All rights reserved.

FLX371

PRINCIPAL DISPLAY PANEL - 50 mL Bag Label

Albumin (Human)
Flexbumin®

25% USP/50ml
Solution for infusion

Takeda

Single-Dose Container
50 mL
NDC 0944-0493-03
Code 2G0201

Each 50 mL contains: 12.5 g albumin from venous plasma in buffered diluent and
is osmotically equivalent to 250 mL of normal human plasma. It has been stabilized
with sodium caprylate and N-acetyltryptophan and heated for 10 hours at 60°C.
The sodium content is 145 ± 15 mEq/L. Contains no preservative. See accompanying
package insert.

Cautions: In patients with marked dehydration, additional fluids must accompany
or follow administration of this product. Check for minute leaks by squeezing bag
firmly. If leaks are found, discard bag as sterility may be impaired. Do not use if
turbid. Do not begin administration more than 4 hours after the container has
been entered. Discard partially used container. The patient and physician should
discuss the risks and benefits of this product.

Rx Only

Recommended storage: Store at room temperature, not to exceed 25°C (77°F).
Protect from freezing.

FLEXBUMIN is a registered trademark of Baxalta Incorporated.
Takeda and are registered trademarks of Takeda
Pharmaceutical Company Limited.

©2024 Takeda Pharmaceutical Company Limited. All rights reserved.

Takeda Pharmaceuticals U.S.A., Inc.
Cambridge, MA 02142 U.S. License No. 1898

PL 2501 Plastic 0762486

PRINCIPAL DISPLAY PANEL - 50 mL Carton Label

Albumin (Human)
Flexbumin®

25% USP/50ml
Solution for infusion

Takeda

12 x 50 mL
Single-Dose
Containers

NDC 0944-0493-01
Code 2G0201

PRINCIPAL DISPLAY PANEL - 100 mL Bag Label

Albumin (Human)
Flexbumin®

25% USP/100ml
Solution for infusion

Takeda

Single-Dose Container
100 mL
NDC 0944-0493-04
Code 2G0012

Each 100 mL contains: 25 g albumin from venous plasma in
buffered diluent and is osmotically equivalent to 500 mL of normal
human plasma. It has been stabilized with sodium caprylate
and N-acetyltryptophan and heated for 10 hours at 60°C. The
sodium content is 145 ± 15 mEq/L. Contains no preservative. See
accompanying package insert.

Cautions: In patients with marked dehydration, additional fluids must
accompany or follow administration of this product. Check for minute
leaks by squeezing bag firmly. If leaks are found, discard bag as sterility
may be impaired. Do not use if turbid. Do not begin administration
more than 4 hours after the container has been entered. Discard
partially used container. The patient and physician should discuss the
risks and benefits of this product.

Rx Only

Recommended storage: Store at room temperature, not to exceed 25°C
(77°F). Protect from freezing.

FLEXBUMIN is a registered trademark of Baxalta Incorporated.
Takeda and are registered trademarks of Takeda
Pharmaceutical Company Limited.

©2024 Takeda Pharmaceutical Company Limited. All rights
reserved.

Takeda Pharmaceuticals U.S.A., Inc.
Cambridge, MA 02142 U.S. License No. 1898

PL 2501 Plastic 0762490

PRINCIPAL DISPLAY PANEL - 100 mL Carton Label

Albumin (Human)
Flexbumin®

25% USP/100ml
Solution for infusion

Takeda

6 x 100 mL
Single-Dose
Containers

NDC 0944-0493-02
Code 2G0012